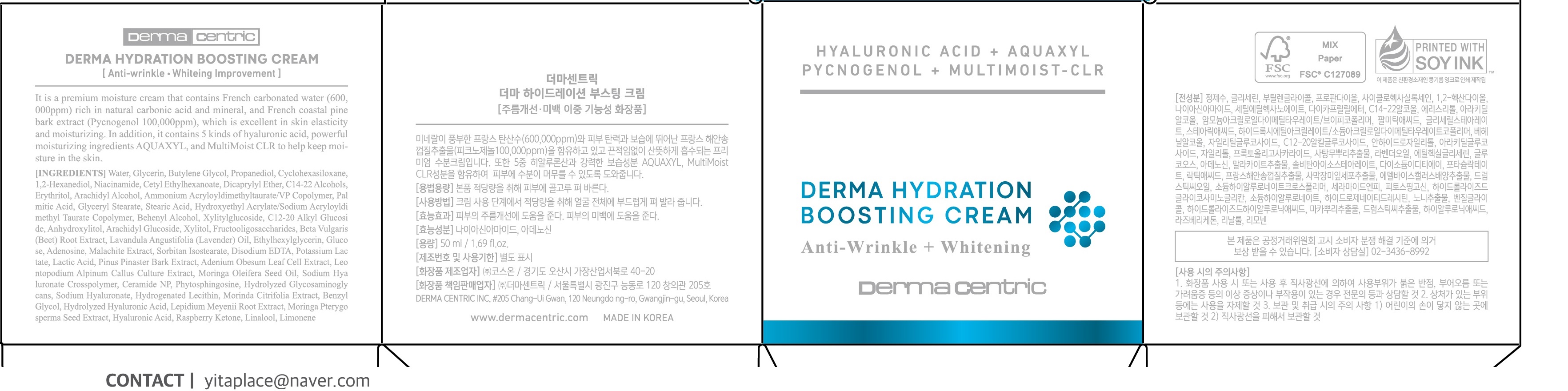 DRUG LABEL: DERMA HYDRATION BOOSTING
NDC: 79593-0008 | Form: CREAM
Manufacturer: DERMA CENTRIC INC
Category: otc | Type: HUMAN OTC DRUG LABEL
Date: 20210328

ACTIVE INGREDIENTS: ADENOSINE 0.04 g/100 mL; NIACINAMIDE 2 g/100 mL
INACTIVE INGREDIENTS: WATER; GLYCERIN

ACTIVE INGREDIENT

niacinamide, adenosine

PURPOSE

anti-wrinkle, whitening improvement

KEEP OUT OF REACH OF THE CHILDREN

WARNINGS

■ For external use only.

■ Do not use in eyes.

■ lf swallowed, get medical help promptly.

■ Stop use, ask doctor lf irritation occurs.

■ Keep out of reach of children.

DOSAGE AND ADMINISTRATION

for external use only

INACTIVE INGREDIENT

Water
Butylene Glycol
1,2-Hexanediol
Water
1,2-Hexanediol
Pinus Pinaster Bark Extract
Water
Propanediol
Glycerin
Cyclohexasiloxane
Dicaprylyl Ether
Cetyl Ethylhexanoate
Niacinamide
Arachidyl Alcohol
Behenyl Alcohol
Arachidyl Glucoside
Glucose
Water
C14-22 Alcohols
C12-20 Alkyl Glucoside
Water
Glucose
Palmitic Acid
Stearic Acid
Xylitylglucoside
Anhydroxylitol
Water
Xylitol
Glucose
Erythritol
Water
Malachite Extract
1,2-Hexanediol
Ammonium Acryloyldimethyltaurate/VP Copolymer
Glyceryl Stearate
Hydroxyethyl Acrylate/Sodium Acryloyldimethyl Taurate Copolymer
Water
Sorbitan Isostearate
Lavandula Angustifolia (Lavender) Oil
Ethylhexylglycerin
Fructooligosaccharides
Beta Vulgaris (Beet) Root Extract
Water
Potassium Lactate
Lactic Acid
Adenosine
Disodium EDTA
Water
1,2-Hexanediol
Moringa Pterygosperma Seed Extract
Water
Butylene Glycol
Adenium Obesum Leaf Cell Extract
1,2-Hexanediol
Water
Butylene Glycol
Leontopodium Alpinum Callus Culture Extract
1,2-Hexanediol
Glycerin
Moringa Oleifera Seed Oil
Ceramide NP
Phytosphingosine
Hydrogenated Lecithin
Water
1,2-Hexanediol
Morinda Citrifolia Extract
Water
1,2-Hexanediol
Lepidium Meyenii Root Extract
Water
Propanediol
Sodium Hyaluronate Crosspolymer
Hydrolyzed Glycosaminoglycans
Glycerin
Sodium Hyaluronate
Benzyl Glycol
Hydrolyzed Hyaluronic Acid
Ethylhexylglycerin
Hyaluronic Acid
Raspberry Ketone

INDICATIONS AND USAGE

apply proper amount to the skin